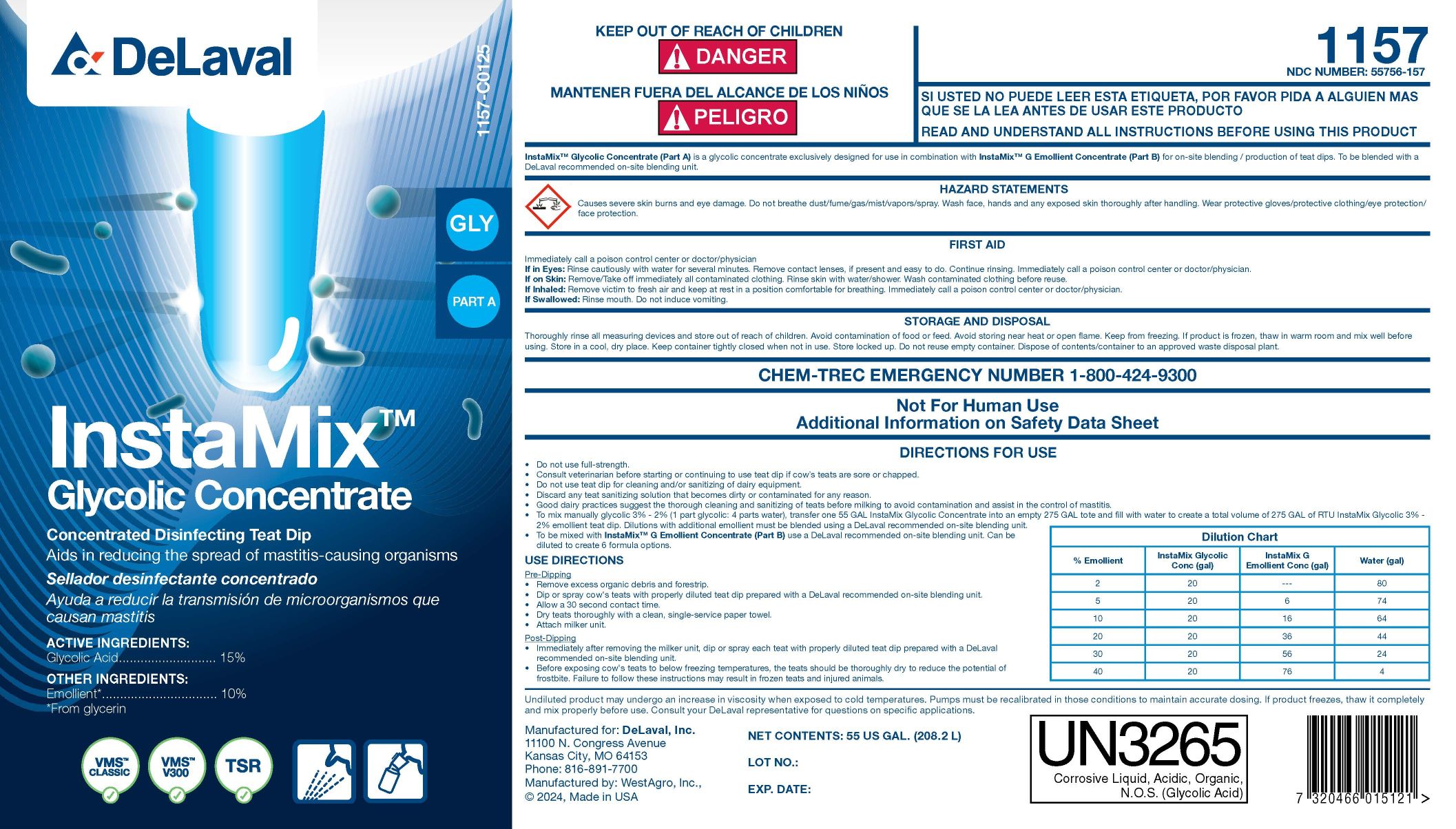 DRUG LABEL: InstaMix Glycolic Concentrate
NDC: 55756-157 | Form: CONCENTRATE
Manufacturer: DeLaval
Category: animal | Type: OTC ANIMAL DRUG LABEL
Date: 20250226

ACTIVE INGREDIENTS: GLYCOLIC ACID 150 g/1 L
INACTIVE INGREDIENTS: GLYCERIN; WATER; XANTHAN GUM; SODIUM CAPRYLYL SULFONATE; SODIUM C14-16 OLEFIN SULFONATE; C9-11 PARETH-8; FD&C BLUE NO. 1; SODIUM HYDROXIDE

InstaMixTM Glycolic Concentrate

PURPOSE

Concentrated Disinfecting Teat Dip

Aids in reducing the spread of mastitis-causing organisms

ACTIVE INGREDIENTS:

Glycolic Acid ................... 15%

OTHER INGREDIENTS:

Emollient* ................... 10%

*From glycerin

KEEP OUT OF REACH OF CHILDREN

! DANGER

WARNINGS

READ AND UNDERSTAND ALL INSTRUCTIONS BEFORE USING THIS PRODUCT

InstaMixTM Glycolic Concentrate (Part A) is a glycolic concentrate exclusively designed for use in combination with InstaMixTM G Emollient Concentrate (Part B) for on-site blending/production of teat dips. To be blended with a DeLaval recommended on-site blending unit.

FIRST AID

Immediately call a poison control center or doctor/physician

If in Eyes: Rinse cautiously with water for several minutes. Remove contact lenses, if present and easy to do. Continue rinsing. Immediately call a poison control center or doctor/physician.

If on Skin: Remove/Take off immediately all contaminated clothing. Rinse skin with water/shower. Wash contaminated clothing before reuse.

If Inhaled: Remove victim to fresh air and keep at rest in a position comfortable for breathing. Immediately call a poison control center or doctor/physician.

If swallowed: Rinse mouth. Do not induce vomiting.

STORAGE AND DISPOSAL

Thoroughly rinse all measuring devices and store out of reach of children. Avoid contamination of food or feed. Avoid storing near heat or open flame. Keep from freezing. If product is frozen, thaw in warm room and mix well before using. Store in a cool, dry space. Keep container tightly closed when not in use. Store locked up. Do not reuse empty container. Dispose of contents/container to an approved waste disposal plant.

CHEM-TREC EMERGENCY NUMBER 1-800-424-9300

WARNINGS AND PRECAUTIONS

Not For Human Use

Additional Information on Safety Data Sheet

INDICATIONS AND USAGE

DIRECTIONS FOR USE

- Do not use full-strength.
- Consult veterinarian before starting or continuing to use teat dip if cow's teats are sore or chapped.
- Do not use teat dip for cleaning and/or sanitizing of dairy equpment.
- Discard any teat sanitizing solution that becomes dirty or contaminated for any reason.
- Good dairy practices suggest the thorough cleaning and sanitizing of teats before milking to avoid contamination and assist in the control of mastitis.
- To mix manually glycolic 3% - 2% (1 part glycolic: 4 parts water), transfer one 55 GAL InstaMix Glycolic Concentrate into an empty 275 GAL tote and fill with water to create a volume to 275 GAL of RTU InstaMix Glycolic 3% - 2% emollient teat dip. Dilutions with additional emollient must be blended using a DeLaval recommended on-site blending unit.
- To be mixed with InstaMixTM G Emollient Concentrate (Part B) using a DeLaval recommended on-site blending unit. Can be diluted to create 6 formula options.

USE DIRECTIONS

Pre-Dipping

- Remove excess organic debris and forestrip.
- Dip or spray cow's teats with properly diluted teat dip prepared with a DeLaval recommended on-site blending unit.
- Allow a 30 second contact time.
- Dry teats thoroughly with a clean, single-service paper towel.
- Attach milker unit.

Post-Dipping

- Immediately after removing the milker unit, dip or spray each teat with properly diluted teat dip prepared with a DeLaval recommended on-site blending unit.
- Before exposing cow's teats to below freezing temperatures, the teats should be thoroughly dry to reduce the potential of frostbite. Failure to follow these instructions may result in frozen teats and injured animals.

Dilution Chart
% Emollient | InstaMix Glycolic Conc (gal) | Instamix G Emollient Conc (gal) | Water (gal)
2 | 20 | --- | 80
5 | 20 | 6 | 74
10 | 20 | 16 | 64
20 | 20 | 36 | 44
30 | 20 | 56 | 24
40 | 20 | 76 | 4

USER SAFETY WARNINGS

UN3265

Corrosive Liquid, Acidic, Organic, N.O.S. (Glycolic Acid)

WARNINGS

HAZARD STATEMENTS

Causes severe skin burns and eye damage. Do not breathe dust/fume/gas/mist/vapors/spray. Wash face, hands and any exposed skin thoroughly after handling. Wear protective gloves/protective clothing/eye protection/face protection.

NET CONTENTS: US GAL. (L)

LOT NO.:

EXP. DATE:

PACKAGE LABEL

Add image transcription here...